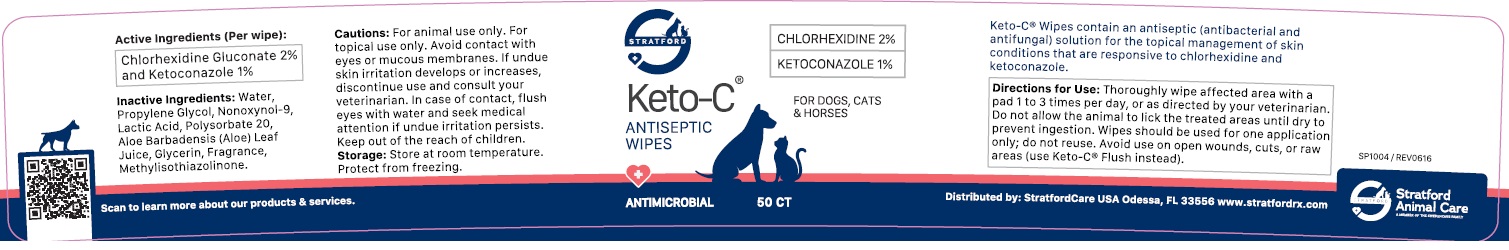 DRUG LABEL: Keto-C ANTISEPTIC WIPES
NDC: 86069-070 | Form: CLOTH
Manufacturer: Stratford Care Usa, Inc.
Category: animal | Type: OTC ANIMAL DRUG LABEL
Date: 20221118

ACTIVE INGREDIENTS: CHLORHEXIDINE 2 g/100 g; KETOCONAZOLE 1 g/100 g
INACTIVE INGREDIENTS: WATER; PROPYLENE GLYCOL; NONOXYNOL-9; LACTIC ACID, UNSPECIFIED FORM; POLYSORBATE 20; ALOE VERA LEAF; GLYCERIN; METHYLISOTHIAZOLINONE

Keto-C® ANTISEPTIC WIPES

Active Ingredients (Per wipe):

Chlorhexidine Gluconate 2% and Ketoconazole 1%

PURPOSE

antibacterial and antifungal

INDICATIONS AND USAGE

Keto-C® Wipes contain an antiseptic (antibacterial and antifungal) solution for the topical management of skin conditions that are responsive to chlorhexidine and ketoconazole.

DOSAGE AND ADMINISTRATION

Directions for Use: Thoroughly wipe affected area with a pad 1 to 3 times per day, or as directed by your veterinarian. Do not allow the animal to lick the treated areas until dry to prevent ingestion. Wipes should be used for one application only; do not reuse. Avoid use on open wounds, cuts, or raw areas (use Keto-C® Flush instead).

INACTIVE INGREDIENT

Inactive Ingredients: Water, Propylene Glycol, Nonoxynol-9, Lactic Acid, Polysorbate 20, Aloe Barbadensis (Aloe) Leaf Juice, Glycerin, Fragrance, Methylisothiazolinone.

PRECAUTIONS

Cautions: For animal use only. For topical use only. Avoid contact with eyes or mucous membranes. If undue skin irritation develops or increases, discontinue use and consult your veterinarian. In case of contact, flush eyes with water and seek medical attention if undue irritation persists. Keep out of the reach of children.

Storage: Store at room temperature. Protect from freezing.

ANTISEPTIC WIPES

FOR DOGS, CATS & HORSES

Distributed by: StratfordCare USA Odessa, FL 33556 www.stratfordrx.com

Stratford Animal Care
A MEMBER OF THE SWEDENCARE FAMILY